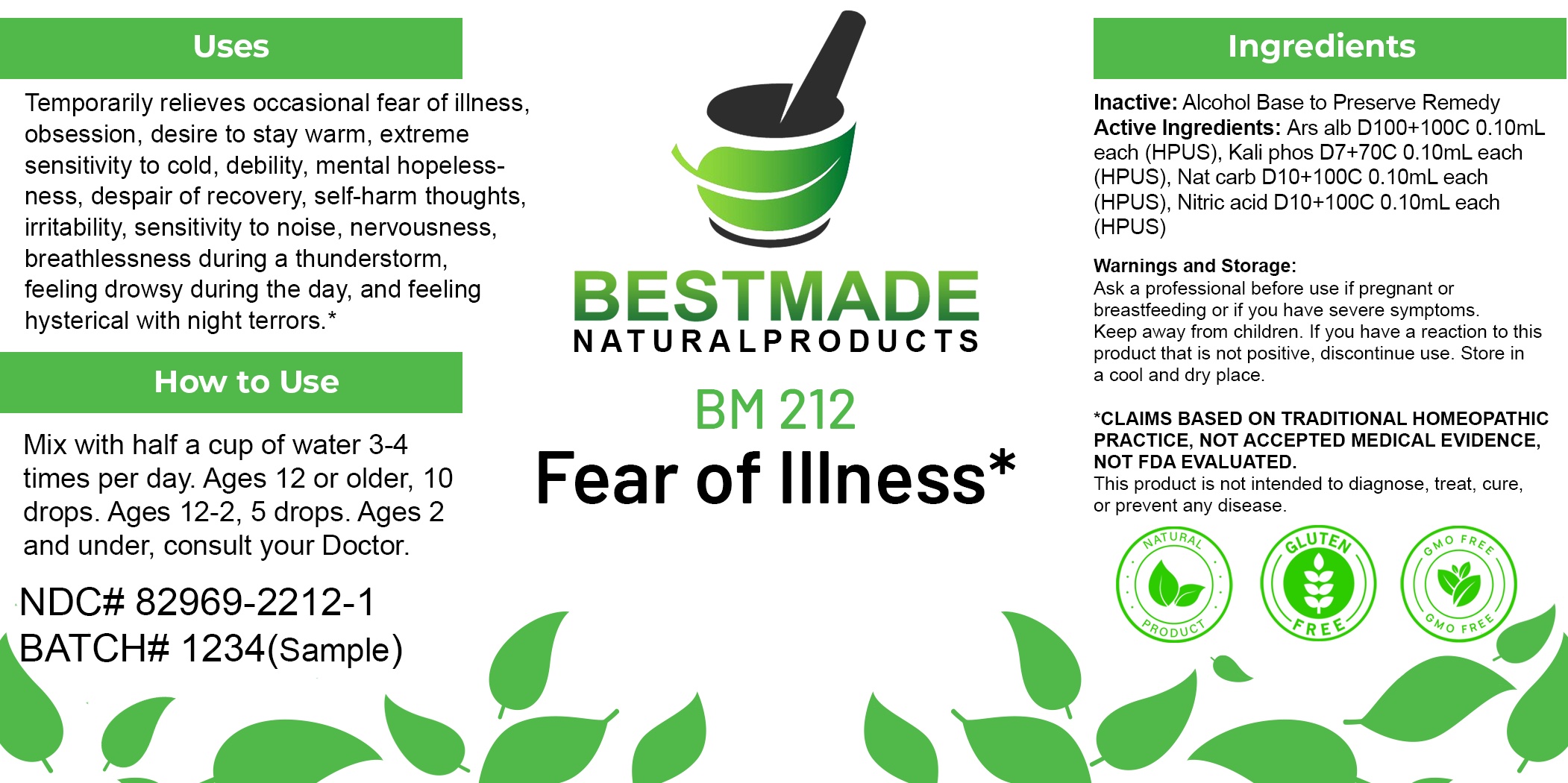 DRUG LABEL: Bestmade Natural Products BM212
NDC: 82969-2212 | Form: LIQUID
Manufacturer: Bestmade Natural Products
Category: otc | Type: HUMAN OTC DRUG LABEL
Date: 20250228

ACTIVE INGREDIENTS: POTASSIUM PHOSPHATE, DIBASIC 30 [hp_C]/30 [hp_C]; ARSENIC TRIOXIDE 30 [hp_C]/30 [hp_C]; SODIUM CARBONATE 30 [hp_C]/30 [hp_C]; NITRIC ACID 30 [hp_C]/30 [hp_C]
INACTIVE INGREDIENTS: ALCOHOL 30 [hp_C]/30 [hp_C]

BM212

DOSAGE AND ADMINISTRATION

How to Use

Mix with half a cup of water 3-4 times per day. Ages 12 or older, 10 drops. Ages 12-2, 5 drops. Ages 2 and under, consult your Doctor.

Inactive:

Alcohol Base to Preserve Product

ACTIVE INGREDIENT

Active Ingredients: Ars alb D100+100C 0.10mL each (HPUS), Kali phos D7+70C 0.10mL each (HPUS), Nat carb D10+100C 0.10mL each (HPUS), Nitric acid D10+100C 0.10mL each (HPUS)

KEEP OUT OF REACH OF CHILDREN

Warnings and Storage:

Ask a professional before use if pregnant or breastfeeding or if you have severe symptoms.

Keep away from children. If you have a reaction to this product that is not positive, discontinue use. Store in a cool and dry place

*CLAIMS BASED ON TRADITIONAL HOMEOPATHIC PRACTICE, NOT ACCEPTED MEDICAL EVIDENCE NOT FDA EVALUATED.
This product is not intended to diagnose, treat, cure, or prevent any disease.

Warnings and Storage:

Ask a professional before use if pregnant or breastfeeding or if you have severe symptoms.

Keep away from children. If you have a reaction to this product that is not positive, discontinue use. Store in a cool and dry place

*CLAIMS BASED ON TRADITIONAL HOMEOPATHIC PRACTICE, NOT ACCEPTED MEDICAL EVIDENCE NOT FDA EVALUATED.
This product is not intended to diagnose, treat, cure, or prevent any disease.

Uses
Temporarily relieves occasional fear of illness, obsession, desire to stay warm, extreme sensitivity to cold, debility, mental hopelessness, despair of recovery, self-harm thoughts, irritability, sensitivity to noise, nervousness, breathlessness during a thunderstorm, feeling drowsy during the day, and feeling hysterical with night terrors.*

Uses
Temporarily relieves occasional fear of illness, obsession, desire to stay warm, extreme sensitivity to cold, debility, mental hopelessness, despair of recovery, self-harm thoughts, irritability, sensitivity to noise, nervousness, breathlessness during a thunderstorm, feeling drowsy during the day, and feeling hysterical with night terrors.*

Entire package label